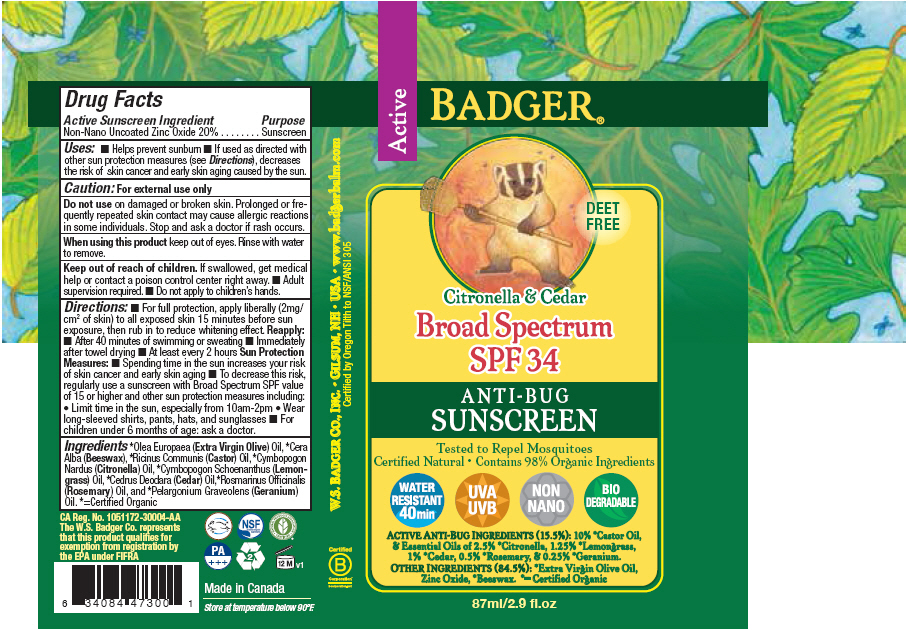 DRUG LABEL: Badger SPF 34 Anti-Bug Sunscreen
NDC: 55143-103 | Form: CREAM
Manufacturer: Norwood Packaging Ltd.
Category: otc | Type: HUMAN OTC DRUG LABEL
Date: 20140113

ACTIVE INGREDIENTS: ZINC OXIDE 20 g/100 mL
INACTIVE INGREDIENTS: OLIVE OIL; YELLOW WAX; CASTOR OIL; CITRONELLA OIL; CEDRUS DEODARA WOOD; ROSEMARY OIL; WEST INDIAN LEMONGRASS OIL; GERANIUM OIL, ALGERIAN TYPE

Badger® SPF 34 Anti-Bug Sunscreen

Drug Facts

Active Sunscreen Ingredient

Non-Nano Uncoated Zinc Oxide 20%

Purpose

Sunscreen

Uses

- Helps prevent sunburn
- If used as directed with other sun protection measures (see Directions), decreases the risk of skin cancer and early skin aging caused by the sun.

Caution

For external use only

Do not use on damaged or broken skin. Prolonged or frequently repeated skin contact may cause allergic reactions in some individuals. Stop and ask a doctor if rash occurs.

When using this product keep out of eyes. Rinse with water to remove.

Keep out of reach of children. If swallowed, get medical help or contact a poison control center right away.

- Adult supervision required.
- Do not apply to children's hands.

Directions

- For full protection, apply liberally (2mg/cm^2 of skin) to all exposed skin 15 minutes before sun exposure, then rub in to reduce whitening effect.

Reapply

- After 40 minutes of swimming or sweating
- Immediately after towel drying
- At least every 2 hours

Sun Protection Measures

- Spending time in the sun increases your risk of skin cancer and early skin aging
- To decrease this risk, regularly use a sunscreen with Broad Spectrum SPF value of 15 or higher and other sun protection measures including:
  - Limit time in the sun, especially from 10am-2pm
  - Wear long-sleeved shirts, pants, hats, and sunglasses
- For children under 6 months of age: ask a doctor.

Ingredients

[=Certified Organic] Olea Europaea (Extra Virgin Olive) Oil, Cera Alba (Beeswax), Ricinus Communis (Castor) Oil, Cymbopogon Nardus (Citronella) Oil, Cymbopogon Schoenanthus (Lemongrass) Oil, Cedrus Deodara (Cedar) Oil,Rosmarinus Officinalis (Rosemary) Oil, and Pelargonium Graveolens (Geranium) Oil.

PRINCIPAL DISPLAY PANEL - 87 ml Tube Label

Active

BADGER®

DEET
FREE

Citronella & Cedar

Broad Spectrum
SPF 34

ANTI-BUG
SUNSCREEN

Tested to Repel Mosquitoes
Certified Natural • Contains 98% Organic Ingredients

WATER
RESISTANT
40 min

UVA
UVB

NON
NANO

BIO
DEGRADABLE

ACTIVE ANTI-BUG INGREDIENTS (15.5%): 10% *Castor Oil,
& Essential Oils of 2.5% *Citronella, 1.25% *Lemongrass,
1% *Cedar, 0.5% *Rosemary, & 0.25% *Geranium.

OTHER INGREDIENTS (84.5%): *Extra Virgin Olive Oil,
Zinc Oxide, *Beeswax. *= Certified Organic

87ml/2.9 fl.oz